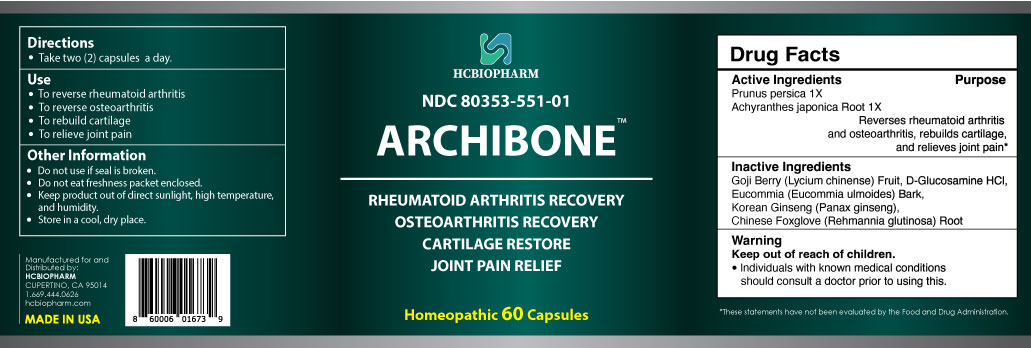 DRUG LABEL: Archibone
NDC: 80353-551 | Form: CAPSULE
Manufacturer: HCBIOPHARM LLC
Category: homeopathic | Type: HUMAN OTC DRUG LABEL
Date: 20250103

ACTIVE INGREDIENTS: ACHYRANTHES JAPONICA ROOT 1 [hp_X]/1 1; PRUNUS PERSICA WHOLE 1 [hp_X]/1 1
INACTIVE INGREDIENTS: REHMANNIA GLUTINOSA ROOT; PANAX GINSENG WHOLE; LYCIUM CHINENSE FRUIT; GLUCOSAMINE HYDROCHLORIDE; EUCOMMIA ULMOIDES BARK

Active Ingredients

Prunus persica 1X, Achyranthes japonica Root 1X

Purpose

Reverses rheumatoid arthritis and osteoarthritis, rebuilds cartilage, and relieves joint pain*

Keep Out of Reach of Children

Directions

Take two (2) capsules a day.

Use

- To reverse rheumatoid arthritis
- To reverse osteoarthritis
- To rebuild cartilage
- To relieve joint pain

Inactive Ingredients

Japanese Cornelian Cherry (Lycium chinense) Fruit, D-Glucosamine HCl, Eucommia (Eucommia ulmoides) Bark, Korean Ginseng (Panax ginseng), Chinese Foxglove (Rehmannia glutinosa) Root

Warning

Individuals with known medical conditions should consult a doctor prior to using this.

Other Information

Do not use if seal is broken.

Do not eat freshness packet enclosed.

Keep product out of direct sunlight, high temperature, and humidity.

Store in a cool, dry place.

Package Label Display

Archibone

RHEUMATOID ARTHRITIS RECOVERY
OSTEOARTHRITIS RECOVERY
CARTILAGE RESTORE
JOINT PAIN RELIEF

Homeopathic 60 Capsules